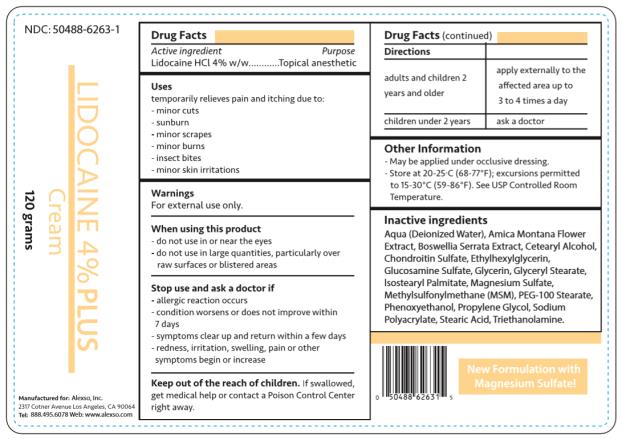 DRUG LABEL: Lidocaine 4 Percent PLUS
NDC: 50488-6263 | Form: CREAM
Manufacturer: Alexso, Inc.
Category: otc | Type: HUMAN OTC DRUG LABEL
Date: 20190212

ACTIVE INGREDIENTS: LIDOCAINE 4 g/100 g
INACTIVE INGREDIENTS: WATER; ARNICA MONTANA FLOWER; INDIAN FRANKINCENSE; CETOSTEARYL ALCOHOL; CHONDROITIN SULFATE (BOVINE); ETHYLHEXYLGLYCERIN; GLUCOSAMINE SULFATE; GLYCERIN; GLYCERYL MONOSTEARATE; ISOSTEARYL PALMITATE; MAGNESIUM SULFATE, UNSPECIFIED FORM; DIMETHYL SULFONE; PEG-100 STEARATE; PHENOXYETHANOL; PROPYLENE GLYCOL; SODIUM POLYACRYLATE (2500000 MW); STEARIC ACID; TROLAMINE

Lidocaine 4 Percent PLUS Cream

Active ingredient

Lidocaine HCl 4% w/w

Purpose

Topical anesthetic

Uses

Temporarily relieves pain and itching due to:

- minor cuts
- sunburn
- minor scrapes
- minor burns
- insect bites
- minor skin irritations

Warnings

For external use only.

When using this product

- do not use in or near the eyes
- do not use in large quantities, particularly over raw surfaces or blistered areas

Stop use and ask a doctor if

- allergic reaction occurs
- condition worsens or does not improve within 7 days
- symptoms clear up and return within a few days
- redness, irritation, swelling, pain or other symptoms begin or increase

Keep out of reach of children.

If swallowed, get medical help or contact a Poison Control Center right away.

Directions

adults and children 2 years and older | apply externally to the affected area up to 3 to 4 times a day
children under 2 years | ask a doctor

Other Information

- May be applied under occlusive dressing.
- Store at 20-25°C (68-77°F); excursions permitted to 15-30°C (59-86°F). See USP Controlled Room Temperature.

Inactive ingredients

Aqua (Deionized Water), Arnica Montana Flower Extract, Boswellia Serrata Extract, Cetearyl Alcohol, Chondroitin Sulfate, Ethylhexylglycerin, Glucosamine Sulfate, Glycerin, Glyceryl Stearate, Isostearyl Palmitate, Magnesium Sulfate, Methylsulfonylmethane (MSM), PEG-100 Stearate, Phenoxyethanol, Propylene Glycol, Sodium Polyacrylate, Stearic Acid, Triethanolamine.

PRINCIPAL DISPLAY PANEL

NDC 50488-6263-1

Lidocaine 4% PLUS Cream

120 grams

Manufactured for: Alexso, Inc.
2317 Cotner Avenue Los Angeles, CA 90064
Tel: 888.495.6078 Web: www.alexso.com

Label